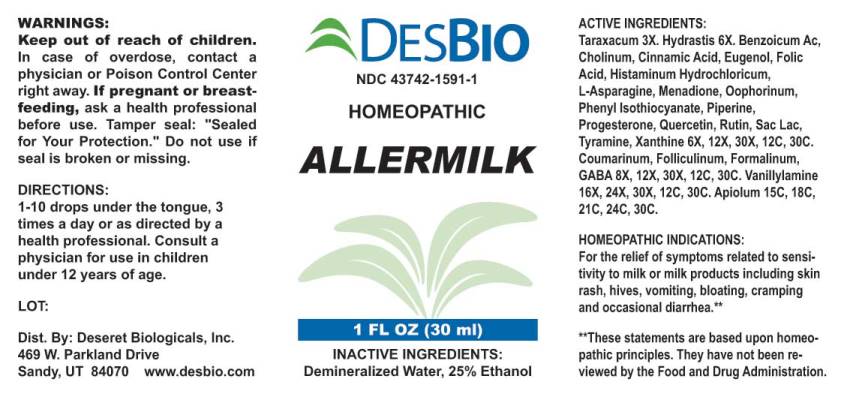 DRUG LABEL: Allermilk
NDC: 43742-1591 | Form: LIQUID
Manufacturer: Deseret Biologicals, Inc.
Category: homeopathic | Type: HUMAN OTC DRUG LABEL
Date: 20230112

ACTIVE INGREDIENTS: TARAXACUM OFFICINALE 3 [hp_X]/1 mL; GOLDENSEAL 6 [hp_X]/1 mL; BENZOIC ACID 6 [hp_X]/1 mL; CHOLINE HYDROXIDE 6 [hp_X]/1 mL; CINNAMIC ACID 6 [hp_X]/1 mL; EUGENOL 6 [hp_X]/1 mL; FOLIC ACID 6 [hp_X]/1 mL; HISTAMINE DIHYDROCHLORIDE 6 [hp_X]/1 mL; ASPARAGINE 6 [hp_X]/1 mL; MENADIONE 6 [hp_X]/1 mL; SUS SCROFA OVARY 6 [hp_X]/1 mL; PHENYL ISOTHIOCYANATE 6 [hp_X]/1 mL; PIPERINE 6 [hp_X]/1 mL; PROGESTERONE 6 [hp_X]/1 mL; QUERCETIN 6 [hp_X]/1 mL; RUTIN 6 [hp_X]/1 mL; LACTOSE, UNSPECIFIED FORM 6 [hp_X]/1 mL; TYRAMINE 6 [hp_X]/1 mL; XANTHINE 6 [hp_X]/1 mL; COUMARIN 8 [hp_X]/1 mL; ESTRONE 8 [hp_X]/1 mL; FORMALDEHYDE 8 [hp_X]/1 mL; .GAMMA.-AMINOBUTYRIC ACID 8 [hp_X]/1 mL; VANILLYLAMINE 16 [hp_X]/1 mL; APIOLE (PARSLEY) 15 [hp_C]/1 mL
INACTIVE INGREDIENTS: WATER; ALCOHOL

Drug Facts:

ACTIVE INGREDIENTS:

Taraxacum Officinale 3X, Hydrastis Canadensis 6X, Benzoicum Acidum 6X, 12X, 30X, 12C, 30C, Cholinum 6X, 12X, 30X, 12C, 30C, Cinnamic Acid 6X, 12X, 30X, 12C, 30C, Eugenol 6X, 12X, 30X, 12C, 30C, Folic Acid 6X, 12X, 30X, 12C, 30C, Histaminum Hydrochloricum 6X, 12X, 30X, 12C, 30C, L-Asparagine 6X, 12X, 30X, 12C, 30C, Menadione 6X, 12X, 30X, 12C, 30C, Oophorinum (Suis) 6X, 12X, 30X, 12C, 30C, Phenyl Isothiocyanate 6X, 12X, 30X, 12C, 30C, Piperine 6X, 12X, 30X, 12C, 30C, Progesterone 6X, 12X, 30X, 12C, 30C, Quercetin 6X, 12X, 30X, 12C, 30C, Rutin 6X, 12X, 30X, 12C, 30C, Saccharum Lactis 6X, 12X, 30X, 12C, 30C, Tyramine 6X, 12X, 30X, 12C, 30C, Xanthine 6X, 12X, 30X, 12C, 30C, Coumarinum 8X, 12X, 30X, 12C, 30C, Folliculinum 8X, 12X, 30X, 12C, 30C, Formalinum 8X, 12X, 30X, 12C, 30C, GABA (Gamma Aminobutyric Acid) 8X, 12X, 30X, 12C, 30C, Vanillylamine 16X, 24X, 30X, 12C, 30C, Apiolum 15C, 18C, 21C, 24C, 30C.

HOMEOPATHIC INDICATIONS:

For the relief of symptoms related to sensitivity to milk or milk products including skin rash, hives, vomiting, bloating, cramping and occasional diarrhea.**

**These statements are based upon homeopathic principles. They have not been reviewed by the Food and Drug Administration.

WARNINGS:

Keep out of reach of children. In case of overdose, contact a physician or Poison Control Center right away.

If pregnant or breast-feeding, ask a health professional before use.

Tamper seal: "Sealed for Your Protection." Do not use if seal is broken or missing.

Keep out of reach of children. In case of overdose, contact a physician or Poison Control Center right away.

DIRECTIONS:

1-10 drops under the tongue, 3 times a day or as directed by a health professional. Consult a physician for use in children under 12 years of age.

HOMEOPATHIC INDICATIONS:

For the relief of symptoms related to sensitivity to milk or milk products including skin rash, hives, vomiting, bloating, cramping and occasional diarrhea.**

**These statements are based upon homeopathic principles. They have not been reviewed by the Food and Drug Administration.

INACTIVE INGREDIENTS:

Demineralized water, 25% Ethanol.

QUESTIONS:

Dist. By: Deseret Biologicals, Inc.

469 W. Parkland Drive

Sandy, UT 84070 www.desbio.com

PACKAGE LABEL DISPLAY:

DESBIO

NDC 43742-1591-1

HOMEOPATHIC

ALLERMILK

1 FL OZ (30 ml)